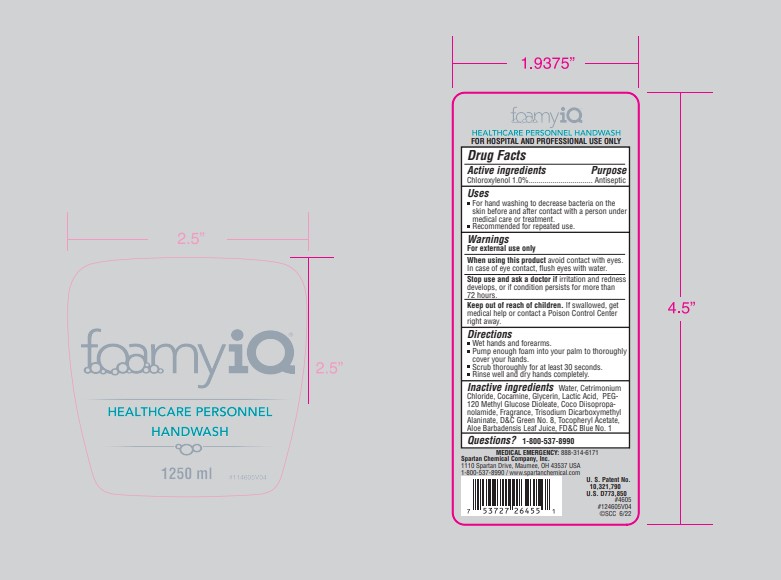 DRUG LABEL: FoamyIQ Healthcare Personnel Handwash
NDC: 64009-203 | Form: SOAP
Manufacturer: Spartan Chemical Company
Category: otc | Type: HUMAN OTC DRUG LABEL
Date: 20231219

ACTIVE INGREDIENTS: CHLOROXYLENOL 10.11 g/1 L
INACTIVE INGREDIENTS: WATER; CETRIMONIUM CHLORIDE; COCAMINE; GLYCERIN; LACTIC ACID, L-; PEG-120 METHYL GLUCOSE DIOLEATE; COCO DIISOPROPANOLAMIDE; TRISODIUM DICARBOXYMETHYL ALANINATE, L-; D&C GREEN NO. 8; .ALPHA.-TOCOPHEROL ACETATE; ALOE VERA LEAF; FD&C BLUE NO. 1

Drug Facts

Active Ingredients

Chloroxylenol 1.0%

Purpose

Antiseptic

Uses

- Healthcare personnel hand wash for hand washing to decrease bacteria on the skin before and after contact with a person under medical care or treatment.
- Recommended for repeated use.

Warnings

- For external use only

When using this product avoid contact with eyes. In case of eye contact, flush eyes with water.

Stop use and ask a doctor if irritation and redness develops, or if condition persists for more than 72 hours.

Keep out of reach of children.

If swallowed, get medical help or contact a Poison Control Center right away.

Directions

- Wet hands and forearms.
- Pump enough foam into your palm to thoroughly cover your hands.
- Scrub thoroughly for at least 30 seconds.
- Rinse well and dry hands completely.

Inactive Ingredients

Water, Cetrimonium Chloride, Cocamine, Glycerin, Lactic Acid, PEG-120 Methyl Glucose Dioleate, Coco Diisopropa- nolamide, Fragrance, Trisodium Dicarboxymethyl Alaninate, D&C Green No. 8, Tocopheryl Acetate, Aloe Barbadensis Leaf Juice, FD&C Blue No. 1

Questions?

1-800-537-8990

Principal Display Panel - 1.25 L Container Label

foamy iQ™

HEALTHCARE PERSONNEL
HANDWASH

#114605V04